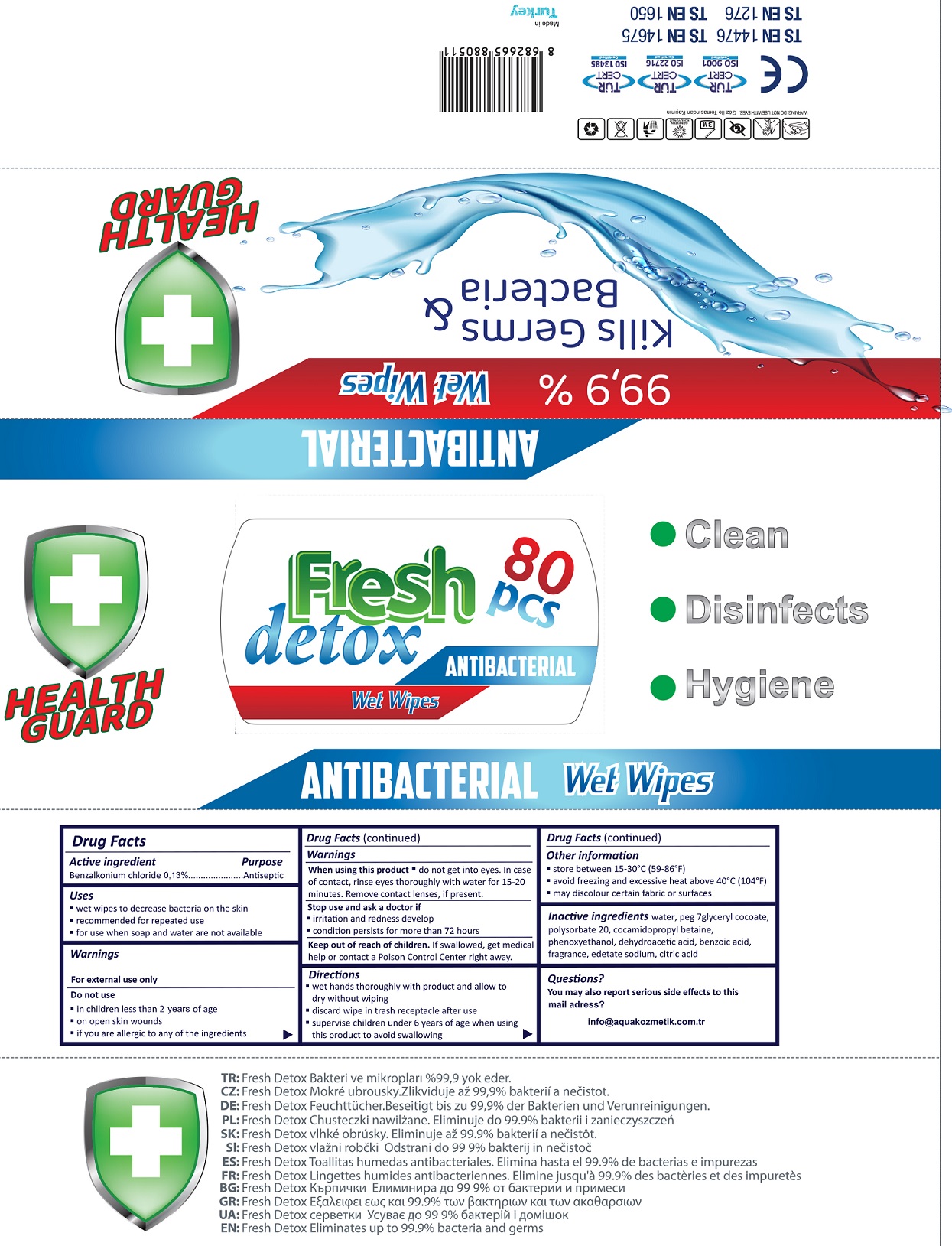 DRUG LABEL: Fresh Detox Antibacterial Wet Wipes
NDC: 79997-001 | Form: CLOTH
Manufacturer: AQUA KOZMETIK DIS TICARET ANONIM SIRKETI
Category: otc | Type: HUMAN OTC DRUG LABEL
Date: 20201230

ACTIVE INGREDIENTS: BENZALKONIUM CHLORIDE 1.3 mg/1 mL
INACTIVE INGREDIENTS: WATER; PEG-7 GLYCERYL COCOATE; POLYSORBATE 20; COCAMIDOPROPYL BETAINE; PHENOXYETHANOL; DEHYDROACETIC ACID; BENZOIC ACID; EDETATE SODIUM; CITRIC ACID MONOHYDRATE

Fresh Detox Antibacterial Wet Wipes

Active ingredient

Benzalkonium chloride 0.13%

Purpose

Antiseptic

Uses

- wet wipes to decrease bacteria on the skin
- recommended for repeated use
- for use when soap and water are not available

Warnings

For external use only

Do not use

- in children less than 2 years of age
- on open skin wounds
- if you are allergic to any of the ingredients

When using this product

do not get into eyes. In case of contact, rinse eyes thoroughly with water for 15-20 minutes. Remove contact lenses, if present.

Stop use and ask a doctor if

- irritation and redness develop
- condition persists for more than 72 hours

Keep out of reach of children.

If swallowed, get medical help or contact a Poison Control Center right away.

Directions

- wet hands thoroughly with product and allow to dry without wiping
- discard wipe in trash receptacle after use
- supervise children under 6 years of age when using this product to avoid swallowing

Other information

- store between 15-30°C (59-86°F)
- avoid freezing and excessive heat above 40°C (104°F)
- may discolour certain fabric or surfaces

Inactive ingredients

water, peg 7glyceryl cocoate, polysorbate 20, cocamidopropyl betaine, phenoxyethanol, dehydroacetic acid, benzoic acid, fragrance, edetate sodium, citric acid

Questions?

You may also report serious side effects to this mail adress?

info@aquakozmetic.com.tr